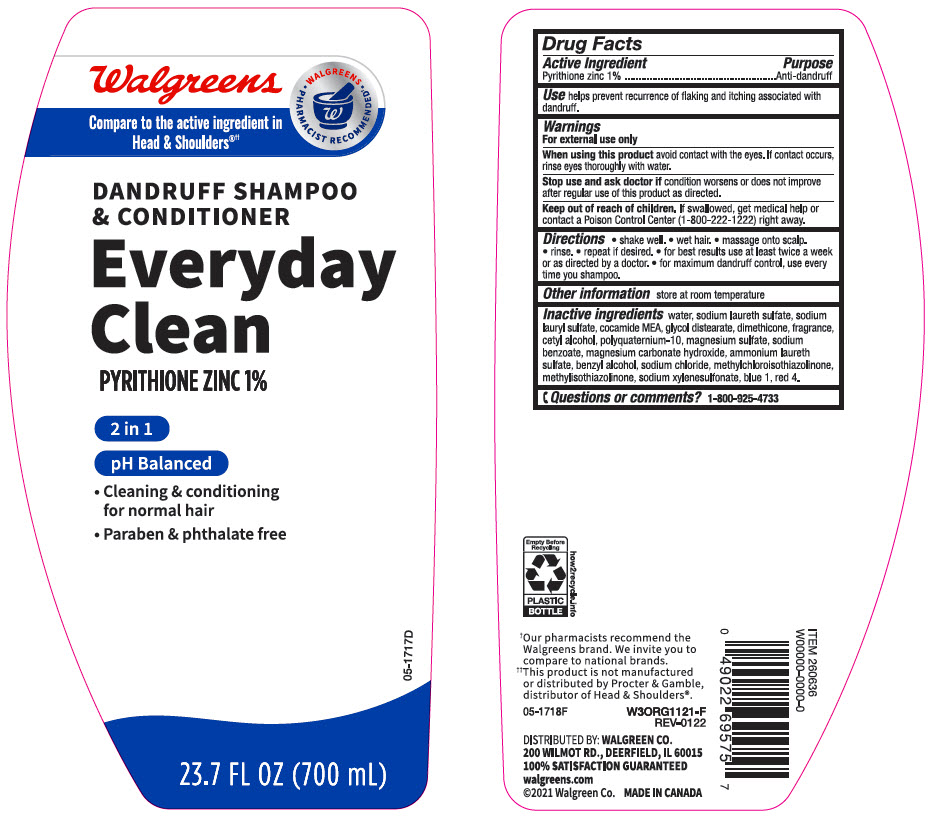 DRUG LABEL: Walgreens Everyday Clean Dandruff
NDC: 0363-2606 | Form: SHAMPOO
Manufacturer: Walgreen Company
Category: otc | Type: HUMAN OTC DRUG LABEL
Date: 20240422

ACTIVE INGREDIENTS: Pyrithione Zinc 10 mg/1 mL
INACTIVE INGREDIENTS: Water; Sodium Laureth-3 Sulfate; Sodium Lauryl Sulfate; Coco Monoethanolamide; Glycol Distearate; Dimethicone; Cetyl Alcohol; Polyquaternium-10 (30000 MPA.S at 2%); Magnesium Sulfate, Unspecified Form; Sodium Benzoate; Magnesium Carbonate Hydroxide; Ammonium Laureth-5 Sulfate; Benzyl Alcohol; Sodium Chloride; Methylchloroisothiazolinone; Methylisothiazolinone; Sodium Xylenesulfonate; FD&C Blue No. 1; FD&C Red No. 4

Walgreens Everyday Clean Dandruff Shampoo & Conditioner
Anti-Dandruff

Drug Facts

Active ingredient

Pyrithione zinc 1 %

Purpose

Anti-dandruff

Use

helps prevent recurrence of flaking and itching associated with dandruff.

Warnings

For external use only.

When using this product avoid contact with the eyes. If contact occurs, rinse eyes thoroughly with water.

Stop use and ask a doctor if condition worsens or does not improve after regular use of this product as directed.

Keep out of reach of children. If swallowed, get medical help or contact a Poison Control Center (1-800-222-1222) right away.

Directions

- shake well
- wet hair
- massage onto scalp
- rinse
- repeat if desired
- for best results use at least twice a week or as directed by a doctor
- for maximum dandruff control, use every time you shampoo.

Other information

store at room temperature

Inactive ingredients

water, sodium laureth sulfate, sodium lauryl sulfate, cocamide MEA, glycol distearate, dimethicone, fragrance, cetyl alcohol, polyquaternium-10, magnesium sulfate, sodium benzoate, magnesium carbonate hydroxide, ammonium laureth sulfate, benzyl alcohol, sodium chloride, methylchloroisothiazolinone, methylisothiazolinone, sodium xylenesulfonate, blue 1, red 4.

Questions or comments?

1-866-925-4733

DISTRIBUTED BY: WALGREEN CO.
200 WILMOT RD., DEERFIELD, IL 60015

PRINCIPAL DISPLAY PANEL - 700 mL Bottle Label

Walgreens

Compare to the active ingredient in
Head & Shoulders®††

• WALGREENS •
PHARMACIST RECOMMENDED

DANDRUFF SHAMPOO
& CONDITIONER

Everyday
Clean
PYRITHIONE ZINC 1%

2 in 1

pH Balanced

- Cleaning & conditioning
  for normal hair
- Paraben & phthalate free

05-1717D

23.7 FL OZ (700 mL)